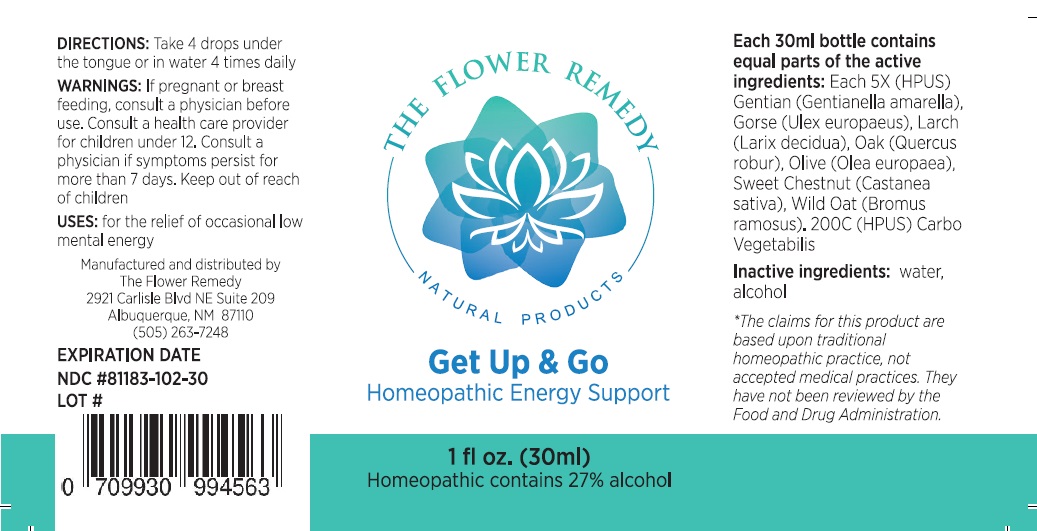 DRUG LABEL: THE FLOWER REMEDY Get Up and Go
NDC: 81183-102 | Form: LIQUID
Manufacturer: The Flower Remedy
Category: homeopathic | Type: HUMAN OTC DRUG LABEL
Date: 20251203

ACTIVE INGREDIENTS: GENTIANELLA AMARELLA FLOWER 5 [hp_X]/30 mL; ULEX EUROPAEUS FLOWER 5 [hp_X]/30 mL; LARIX DECIDUA FLOWERING TOP 5 [hp_X]/30 mL; QUERCUS ROBUR FLOWER 5 [hp_X]/30 mL; OLEA EUROPAEA FLOWER 5 [hp_X]/30 mL; CASTANEA SATIVA FLOWER 5 [hp_X]/30 mL; BROMUS RAMOSUS FLOWER 5 [hp_X]/30 mL; ACTIVATED CHARCOAL 200 [hp_C]/30 mL
INACTIVE INGREDIENTS: WATER; ALCOHOL

THE FLOWER REMEDY NATURAL PRODUCTS Get Up & Go

Active Ingredients:

Each 30ml bottle contains equal parts of the active ingredients:
Each 5X (HPUS) Gentian (Gentianella amarella), Gorse (Ulex europaeus), Larch (Larix decidua), Oak (Quercus robur), Olive (Olea europaea), Sweet Chestnut (Castanea sativa), Wild Oat (Bromus ramosus), 200C (HPUS) Carbo Vegetabilis

Purpose:

Energy Support

USES:

for the relief of occasional low mental energy

DIRECTIONS:

Take 4 drops under the tongue or in water 4 times daily

WARNINGS:

If pregnant or breast feeding, consult a physician before use. Consult a health care provider for children under 12. Consult a physician if symptoms persist for more than 7 days.

Keep out of reach of children.

Inactive ingredients:

water, alcohol

THE FLOWER REMEDY
NATURAL PRODUCTS

Homeopathic Energy Support

Homeopathic contains 27% alcohol

*The claims for this product are based upon traditional homeopathic practice, not accepted medical practices. They have not been reviewed by the Food and Drug Administration.

Manufactured and distributed by
The Flower Remedy
2921 Carlisle Blvd NE Suite 209
Albuquerque, NM 87110
(505) 263-7248